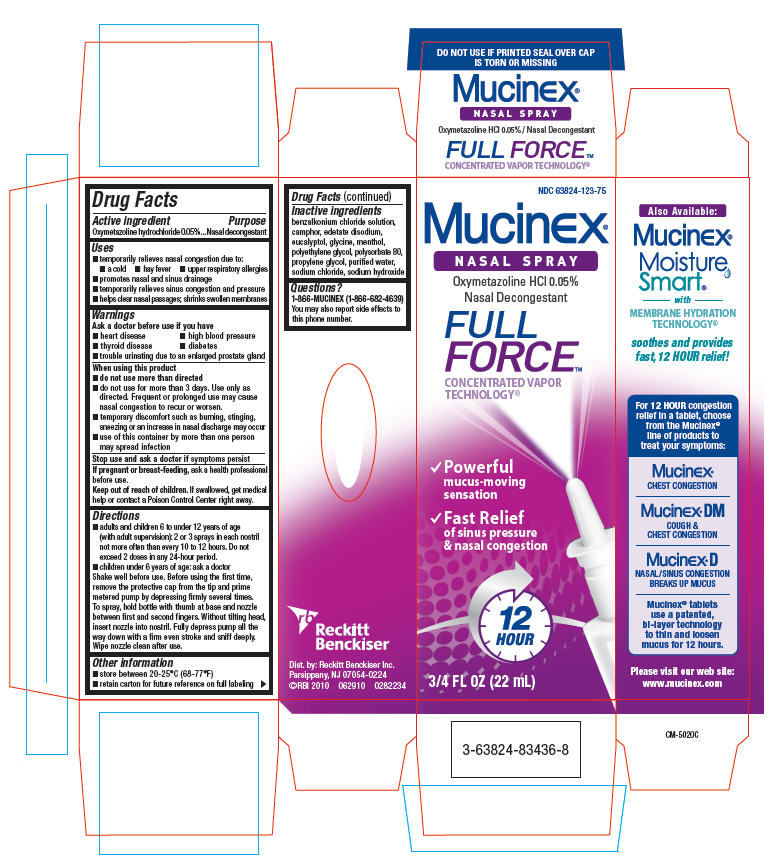 DRUG LABEL: Mucinex
NDC: 63824-123 | Form: SOLUTION
Manufacturer: Reckitt Benckiser, Inc.
Category: otc | Type: HUMAN OTC DRUG LABEL
Date: 20101007

ACTIVE INGREDIENTS: Oxymetazoline Hydrochloride 0.5 mg/1 mL
INACTIVE INGREDIENTS: benzalkonium chloride; camphor (synthetic); edetate disodium; eucalyptol; glycine; menthol; polyethylene glycol; polysorbate 80; propylene glycol; water; sodium chloride; sodium hydroxide

Mucinex®
NASAL SPRAY
FULL FORCE

Drug Facts

Active ingredient

Oxymetazoline hydrochloride 0.05%

Purpose

Nasal decongestant

Uses

- temporarily relieves nasal congestion due to:
  - a cold
  - hay fever
  - upper respiratory allergies
- promotes nasal and sinus drainage
- temporarily relieves sinus congestion and pressure
- helps clear nasal passages; shrinks swollen membranes

Warnings

Ask a doctor before use if you have

- heart disease
- high blood pressure
- thyroid disease
- diabetes
- trouble urinating due to an enlarged prostate gland

When using this product

- do not use more than directed
- do not use for more than 3 days. Use only as directed. Frequent or prolonged use may cause nasal congestion to recur or worsen.
- temporary discomfort such as burning, stinging, sneezing or an increase in nasal discharge may occur
- use of this container by more than one person may spread infection

Stop use and ask a doctor if symptoms persist

PREGNANCY OR BREAST FEEDING

If pregnant or breast-feeding, ask a health professional before use.

Keep out of reach of children. If swallowed, get medical help or contact a Poison Control Center right away.

Directions

- adults and children 6 to under 12 years of age (with adult supervision): 2 or 3 sprays in each nostril not more often than every 10 to 12 hours. Do not exceed 2 doses in any 24-hour period.
- children under 6 years of age: ask a doctor

Shake well before use. Before using the first time, remove the protective cap from the tip and prime metered pump by depressing firmly several times. To spray, hold bottle with thumb at base and nozzle between first and second fingers. Without tilting head, insert nozzle into nostril. Fully depress pump all the way down with a firm even stroke and sniff deeply. Wipe nozzle clean after use.

Other information

- store between 20-25°C (68-77°F)
- retain carton for future reference on full labeling

Inactive ingredients

benzalkonium chloride solution, camphor, edetate disodium, eucalyptol, glycine, menthol, polyethylene glycol, polysorbate 80, propylene glycol, purified water, sodium chloride, sodium hydroxide

Questions?

1-866-MUCINEX (1-866-682-4639)

You may also report side effects to this phone number.

Dist. by: Reckitt Benckiser Inc.
Parsippany, NJ 07054-0224

PRINCIPAL DISPLAY PANEL - 22 mL Bottle Carton

NDC 63824-123-75

Mucinex®
NASAL SPRAY

Oxymetazoline HCl 0.05%
Nasal Decongestant

FULL
FORCE™
CONCENTRATED VAPOR
TECHNOLOGY®

✓ Powerful
  mucus-moving
  sensation
✓ Fast Relief
  of sinus pressure
  & nasal congestion

12
HOUR

3/4 FL OZ (22 mL)